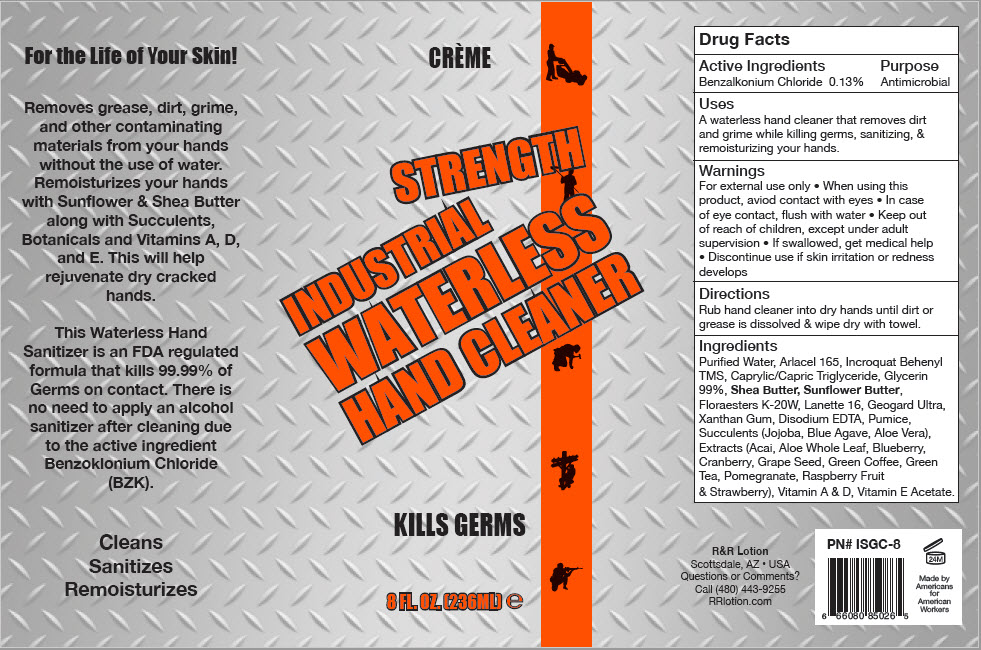 DRUG LABEL: Industrial Strength Waterless Hand Cleaner
NDC: 59555-302 | Form: LOTION
Manufacturer: R & R Lotion, Inc
Category: otc | Type: HUMAN OTC DRUG LABEL
Date: 20210115

ACTIVE INGREDIENTS: Benzalkonium Chloride 1.3 mg/1 mL
INACTIVE INGREDIENTS: water; Xanthan Gum; Calcium Gluconate; Sodium Benzoate; Gluconolactone; Behentrimonium Methosulfate; Cetostearyl Alcohol; Glyceryl 1-Stearate; PEG-100 Stearate; Cetyl Alcohol; Medium-Chain Triglycerides; Shea Butter; .Alpha.-Tocopherol; Glycerin; Potassium Hydrolyzed JOJOBA Esters; cholecalciferol; vitamin A; Pumice

Industrial Strength Waterless Hand Cleaner

Drug Facts

Active Ingredients

Benzalkonium Chloride 0.13%

Purpose

Antimicrobial

Uses

A waterless hand cleaner that removes dirt and grime while killing germs, sanitizing, & remoisturizing your hands.

Warnings

For external use only

- When using this product, aviod contact with eyes
- In case of eye contact, flush with water

- Keep out of reach of children, except under adult supervision
- If swallowed, get medical help
- Discontinue use if skin irritation or redness develops

Directions

Rub hand cleaner into dry hands until dirt or grease is dissolved & wipe dry with towel.

Ingredients

Purified Water, Arlacel 165, Incroquat Behenyl TMS, Caprylic/Capric Triglyceride, Glycerin 99%, Shea Butter, Sunflower Butter, Floraesters K-20W, Lanette 16, Geogard Ultra, Xanthan Gum, Disodium EDTA, Pumice, Succulents (Jojoba, Blue Agave, Aloe Vera), Extracts (Acai, Aloe Whole Leaf, Blueberry, Cranberry, Grape Seed, Green Coffee, Green Tea, Pomegranate, Raspberry Fruit & Strawberry), Vitamin A & D, Vitamin E Acetate.

Questions or Comments?

Call (480) 443-9255

PRINCIPAL DISPLAY PANEL - 236 ML Bottle Label

CRÈME

STRENGTH
INDUSTRIAL
WATERLESS
HAND CLEANER

KILLS GERMS

8 FL. OZ. (236ML) e